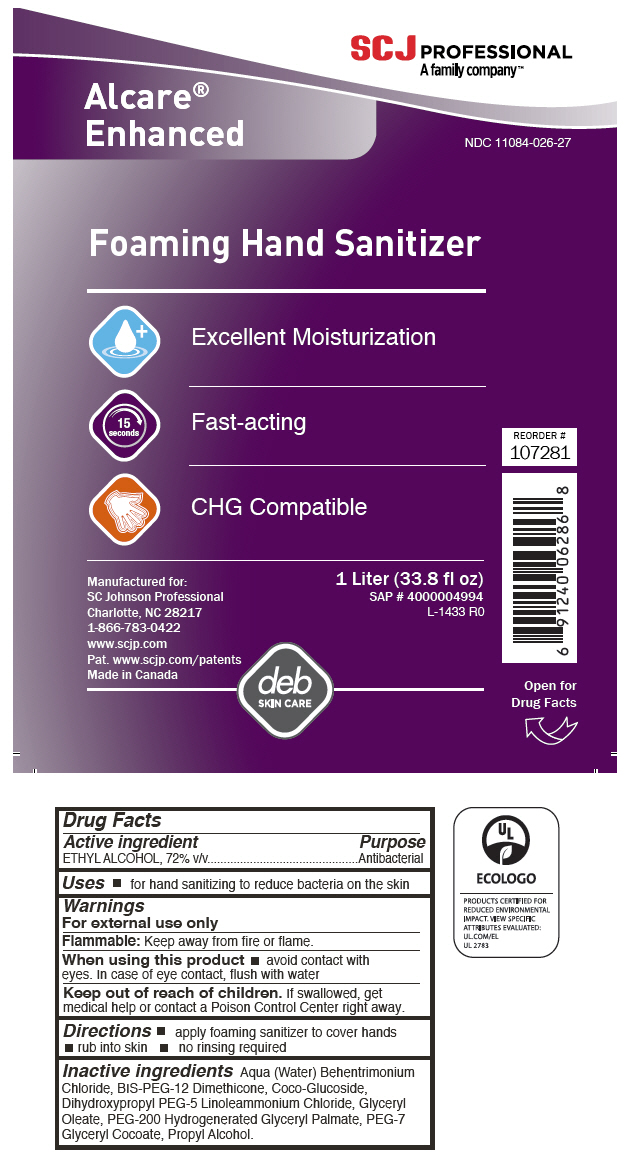 DRUG LABEL: Alcare Enhanced Foaming Hand Sanitizer
NDC: 11084-026 | Form: LIQUID
Manufacturer: SC Johnson Professional USA Inc.
Category: otc | Type: HUMAN OTC DRUG LABEL
Date: 20241213

ACTIVE INGREDIENTS: ALCOHOL 65 g/100 mL
INACTIVE INGREDIENTS: WATER; BEHENTRIMONIUM CHLORIDE; PROPYL ALCOHOL; BIS-PEG-12 DIMETHICONE (500 MPA.S); COCO-GLUCOSIDE; PEG-7 GLYCERYL COCOATE; GLYCERYL OLEATE; PEG-200 HYDROGENATED GLYCERYL PALMATE; DIHYDROXYPROPYL PEG-5 LINOLEAMMONIUM CHLORIDE

Alcare® Enhanced Foaming Hand Sanitizer

Drug Facts

Active ingredient

ETHYL ALCOHOL, 72% v/v

Purpose

Antibacterial

Uses

- for hand sanitizing to reduce bacteria on the skin

Warnings

For external use only

Flammable

Keep away from fire or flame.

When using this product

- avoid contact with eyes. In case of eye contact, flush with water

Keep out of reach of children. If swallowed, get medical help or contact a Poison Control Center right away.

Directions

- apply foaming sanitizer to cover hands
- rub into skin
- no rinsing required

Inactive ingredients

Aqua (Water) Behentrimonium Chloride, BIS-PEG-12 Dimethicone, Coco-Glucoside, Dihydroxypropyl PEG-5 Linoleammonium Chloride, Glyceryl Oleate, PEG-200 Hydrogenerated Glyceryl Palmate, PEG-7 Glyceryl Cocoate, Propyl Alcohol.

PRINCIPAL DISPLAY PANEL - 1 Liter Bottle Label

SCJ PROFESSIONAL
A family company™

Alcare®
Enhanced

NDC 11084-026-27

Foaming Hand Sanitizer

Excellent Moisturization

15
seconds

Fast-acting

CHG Compatible

REORDER #
107281

Manufactured for:
SC Johnson Professional
Charlotte, NC 28217
1-866-783-0422
www.scjp.com
Pat. www.scjp.com/patents
Made in Canada

1 Liter (33.8 fl oz)
SAP # 4000004994
L-1433 R0

deb
SKIN CARE

Open for
Drug Facts